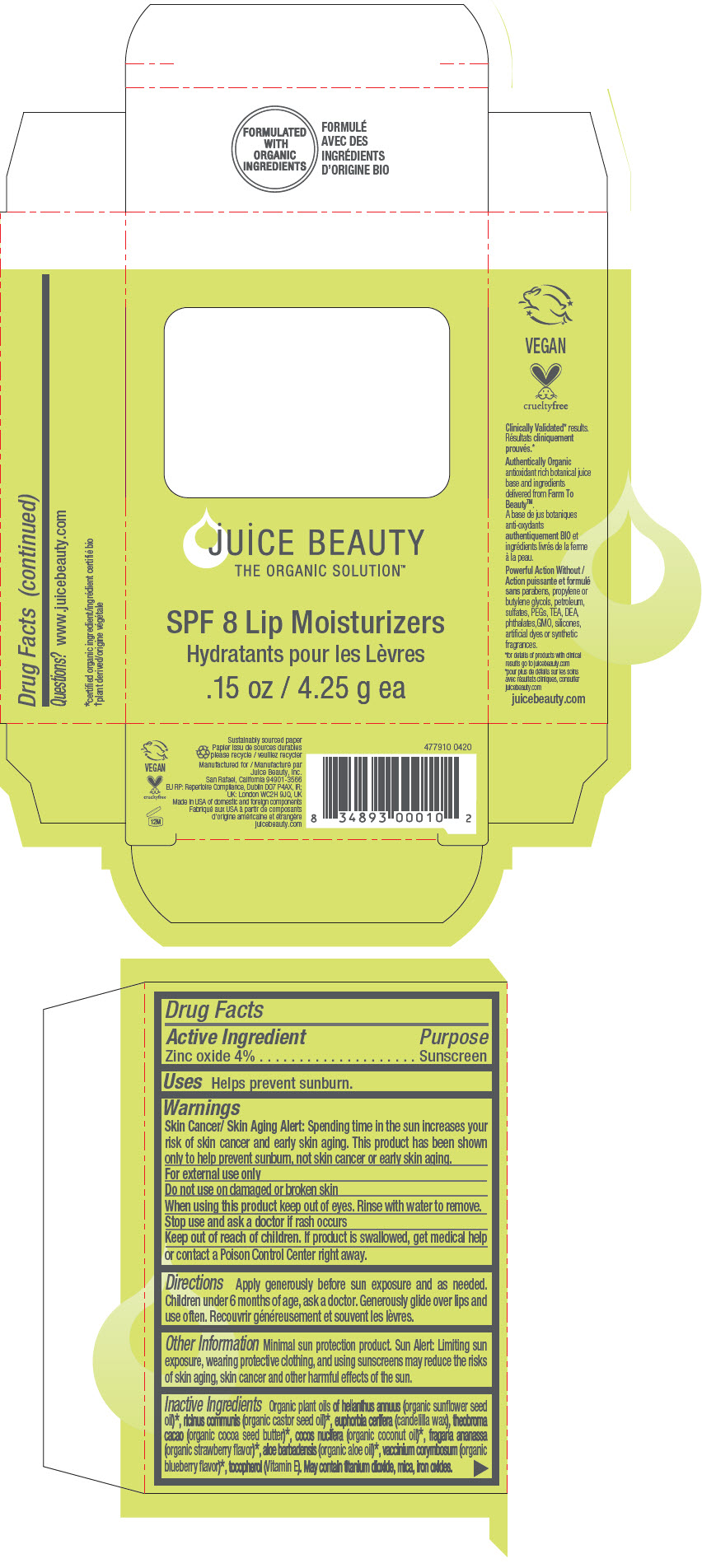 DRUG LABEL: SPF 8 Lip Moisturizers
NDC: 55165-0201 | Form: KIT | Route: TOPICAL
Manufacturer: Juice Beauty
Category: otc | Type: HUMAN OTC DRUG LABEL
Date: 20230105

ACTIVE INGREDIENTS: Zinc Oxide 4 g/100 g; Zinc Oxide 4 g/100 g; Zinc Oxide 4 g/100 g
INACTIVE INGREDIENTS: Sunflower Oil; Candelilla Wax; COCOA BUTTER; Coconut Oil; Castor Oil; FERRIC OXIDE RED; ALOE VERA LEAF; TOCOPHEROL	; Mica; Titanium Dioxide; Sunflower Oil; Candelilla Wax; COCOA BUTTER; Coconut Oil; Castor Oil; ALOE VERA LEAF; TOCOPHEROL	; Sunflower Oil; Candelilla Wax; COCOA BUTTER; Coconut Oil; Castor Oil; FERRIC OXIDE RED; ALOE VERA LEAF; TOCOPHEROL	; Mica; Titanium Dioxide

SPF 8 Lip Moisturizers

Drug Facts

Active Ingredient

Zinc oxide 4%

Purpose

Sunscreen

Uses

Helps prevent sunburn.

Warnings

Skin Cancer/ Skin Aging Alert

Spending time in the sun increases your risk of skin cancer and early skin aging. This product has been shown only to help prevent sunburn, not skin cancer or early skin aging.

For external use only

Do not use on damaged or broken skin

When using this product keep out of eyes. Rinse with water to remove.

Stop use and ask a doctor if rash occurs

Keep out of reach of children. If product is swallowed, get medical help or contact a Poison Control Center right away.

Directions

Apply generously before sun exposure and as needed. Children under 6 months of age, ask a doctor. Generously glide over lips and use often.

Other Information

Minimal sun protection product. Sun Alert: Limiting sun exposure, wearing protective clothing, and using sunscreens may reduce the risks of skin aging, skin cancer and other harmful effects of the sun.

Inactive Ingredients

Organic plant oils of helianthus annuus (organic sunflower seed oil) [certified organic ingredient] , ricinus communis (organic castor seed oil), euphorbia cerifera (candelilla wax), theobroma cacao (organic cocoa seed butter), cocos nucifera (organic coconut oil), fragaria ananassa (organic strawberry flavor), aloe barbadensis (organic aloe oil), vaccinium corymbosum (organic blueberry flavor), tocopherol (Vitamin E). May contain titanium dioxide, mica, iron oxides.

Questions?

www.juicebeauty.com

PRINCIPAL DISPLAY PANEL - Kit Carton

juice BEAUTY
THE ORGANIC SOLUTION™

SPF 8 Lip Moisturizers
.15 oz / 4.25 g ea